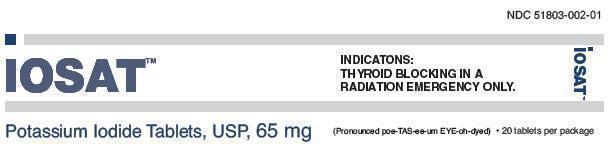 DRUG LABEL: IOSAT
NDC: 51803-002 | Form: TABLET
Manufacturer: Anbex Inc.
Category: otc | Type: HUMAN OTC DRUG LABEL
Date: 20251003

ACTIVE INGREDIENTS: POTASSIUM IODIDE 65 mg/1 1
INACTIVE INGREDIENTS: CELLULOSE, MICROCRYSTALLINE; MAGNESIUM STEARATE; SILICON DIOXIDE; SODIUM THIOSULFATE ANHYDROUS

IOSAT™ - (Potassium Iodide Tablets, USP, 65 mg)

Active Ingredients (in each tablet)

Potassium iodide 65 mg

Purpose

Thyroid blocking

Uses

Helps prevent radioactive iodine from getting into the thyroid gland during a nuclear radiation emergency. Use along with other emergency measures recommended by public officials.

Warnings

Allergy alert:Iodine may cause an allergic reaction with 1 or more of the following symptoms:

- shortness of breath or wheezing
- swelling
- skin rash
- trouble breathing, speaking or swallowing
- fever and joint pain

Do not useif you have

- ever had an allergic reaction to iodine
- nodular thyroid disease with heart disease
- hypocomplementemic vasculitis
- dermatitis herpetiformis

Stop use and ask a doctor ifyou have

- an allergic reaction. Get medical help right away if you have trouble breathing, speaking or swallowing; shortness of breath; wheezing; swelling of the mouth, tongue or throat; or rash.
- irregular heartbeat or chest pain. Get medical help right away.
- swelling of the hands or feet, fever, or joint pain.

Keep out of reach of children.

In case of overdose, get medical help or contact a Poison Control Center right away.

Directions

- use as directed by public officials in the event of a nuclear radiation emergency
- do not take more than 1 dose in 24 hours
- tablets can be whole or crushed and mixed in milk, baby formula, water, orange juice, flat soda like cola, or raspberry syrup

The liquid mixture should be given to infants, young children, and others who cannot swallow tablets; see consumer package insert on how to make a liquid mixture.

Age | Dose
Adults over 18 years | 2 tablets (whole or crushed) daily (130 mg)
Children over 12 years to 18 years who weigh at least 150 pounds | 2 tablets (whole or crushed) daily (130 mg)
Children over 12 years to 18 years who weigh less than 150 pounds | 1 tablet (whole or crushed) daily (65 mg)
Children over 3 years to 12 years | 1 tablet (whole or crushed) daily (65 mg)
Children over 1 month to 3 years | 1/2 tablet (crushed) 32.5 mg daily as directed in the consumer package insert
Birth to 1 month | 16.25 mg daily as directed in the consumer package insert

- If pregnant, breastfeeding, have a baby up to 1 month of age or have thyroid disease (except nodular thyroid disease with heart disease), take as directed above and contact a doctor as soon as possible.

Other Information

- store at 20-25°C (68-77°F)
- keep dry and foil intact
- protect from light
- do not throw away consumer package insert

Inactive ingredients

magnesium stearate, microcrystalline cellulose, silica gel, sodium thiosulfate

Questions or Comments?

call toll free 1-833-467-2854

Distributed by:

ANBEX INC.
1812 West Sunset Blvd, Suite 1A-618
St George, UT 84770
(833) 467-2854

www.anbex.com• www.iosat.com

Consumer Package Insert

IOSAT™

(Potassium Iodide Tablets USP, 65 mg)
(Abbreviated KI)

Take potassium iodide (KI) only when public officials tell you. In a nuclear radiation emergency, radioactive iodine could be released into the air. KI protects only the thyroid gland from uptake of radioactive iodine. Therefore, KI should be used along with other emergency measures that will be recommended to you by public officials. If you are told to take this medicine, take it 1 time every 24 hours. Do not take it more often. More KI will not help you. Too much KI may increase the chances of side effects. Do not take this medicine if you know you are allergic to iodine (see SIDE EFFECTS below).

DESCRIPTION

Each white, round, cross-scored—the name IOSAT stamped on one side—tablet contains 65 mg of potassium iodide.

INDICATIONS

IOSAT™(Potassium Iodide tablets, USP) is a thyroid blocking medicine that is used in a nuclear radiation emergency only.

DIRECTIONS FOR USE

Use only as directed by public officials if a nuclear radiation emergency happens.

Age | Dose
Adults over 18 years | 2 tablets (whole or crushed) every day (130 mg)
Children over 12 years to 18 years who weigh at least 150 pounds | 2 tablets (whole or crushed) every day (130 mg)
Children over 12 years to 18 years who weigh less than 150 pounds | 1 tablet (whole or crushed) or 8 teaspoonfuls every day (65 mg)
Children over 3 years to 12 years | 1 tablet (whole or crushed) or 8 teaspoonfuls every day (65 mg)
Children over 1 month to 3 years | 4 teaspoonfuls every day (32.5 mg)
Birth to 1 month | 2 teaspoonfuls every day (16.25 mg)

Tablets can be crushed and mixed in many liquids. To take the tablet in liquid solution, use dosing directions under Making a Potassium Iodide Liquid Mixture.

Take KI every day (every 24 hours) as directed by public officials. Do not take more than 1 dose in 24 hours. More will not help you. Too much medicine may increase the chances of side effects.

Making a Potassium Iodide Liquid Mixture:

1. Put one65 mg KI tablet into a small bowl and grind it into a fine powder using the back of a metal teaspoon against the inside of the bowl. The powder should not have any large pieces.
2. Add 4 teaspoonfuls of water to the crushed KI powder in the bowl and mix until the KI powder is dissolved in the water.
3. Take the KI water mixture solution made in step 2 and mix it with 4 teaspoonfuls of low fat white or chocolate milk, orange juice, flat soda, raspberry syrup, or infant formula.
4. The KI liquid mixture will keep for up to 7 days in the refrigerator. It is recommended that the KI liquid mixture be prepared weekly. Throw away unused portions.

The amount of KI (65 mg tablet) in the drink when mixed as described above is 8.125 mg per teaspoonful. The number of teaspoonfuls of the drink to give your child depends on your child’s age as described in the following table:

Child's Age | Give your child this amount in teaspoonfuls
Over 12 years to 18 years who weigh less than 150 pounds | 8 teaspoonfuls will give you a 65 mg dose
Over 3 years to 12 years old | 8 teaspoonfuls will give you a 65 mg dose
Over 1 month to 3 years old | 4 teaspoonfuls will give you a 32.5 mg dose
Birth to 1 month | 2 teaspoonful will give you a 16.25 mg dose

Note: This is the amount to give your child for onesingle dose in teaspoonfuls(not tablespoonfuls). You should give your child one dose each day as recommended by the public officials.

Pregnant or breastfeeding women, or babies under 1 month of age:Take as directed above and call a doctor as soon as possible. Repeat dosing should be avoided. It is recommended that thyroid function be checked in babies less than 1 month of age that take KI. Women who are pregnant or breastfeeding should also be checked by a doctor if repeat dosing is necessary. Although these precautions should be taken, the benefits of short-term use of KI to block uptake of radioactive iodine by the thyroid gland far exceed its chances of side effects.

Patients with thyroid disease:If you have both a nodular thyroid condition such as multinodular goiter with heart disease, you should not take KI. Patients with other thyroid conditions may take KI as directed above, but call a doctor if you need to take KI for more than a few days.

WARNING

People who are allergic to iodine, have dermatitis herpetiformis or hypocomplementemic vasculitis, or have nodular thyroid disease with heart disease should not take KI. Keep out of the reach of children. In case of an allergic reaction (difficulty breathing, speaking or swallowing; wheezing; shortness of breath or swelling of the mouth or throat), call 911 or get medical care right away. In case of overdose, get medical help or call a Poison Control Center right away.

HOW POTASSIUM IODIDE WORKS

Certain forms of iodine help your thyroid gland work right. Most people get the iodine they need from foods like iodized salt or fish. The thyroid can “store” or hold only a certain amount of iodine.

In nuclear radiation emergency, radioactive iodine may be released in the air. This material may be breathed or swallowed. It may enter the thyroid gland and damage it. The damage would probably not show itself for years. Children are most likely to have thyroid damage.

If you take KI, it will block or reduce the chances that radioactive iodine will enter your thyroid gland.

WHO SHOULD NOT TAKE POTASSIUM IODIDE

People should avoid KI if they are allergic to iodine, have dermatitis herpetiformis or hypocomplementemic vasculitis, or have nodular thyroid disease with heart disease, because these conditions may increase the chances of side effects to iodine.

HOW AND WHEN TO TAKE POTASSIUM IODIDE

KI should be taken as soon as possible after public officials tell you. If you are told to repeat the dose, you should take the second dose 24 hours after the first dose. Do not take it sooner. More KI will not help you because the thyroid can “hold” only certain amounts of iodine. Taking more than 1 dose per day will increase the chances of side effects. The public officials will tell you how many days to take KI. You should take KI until the chances of major exposure to radioactive iodine by breathing or swallowing stops.

SIDE EFFECTS

Short-term use of KI at the recommended dose is safe. You should not take this drug for longer than you are told.

Possible side effects include: swelling of the salivary glands, nausea, vomiting, diarrhea, stomach ache, fever, headache, metallic taste, and allergic reactions. Allergic reaction can include

- skin rashes such as hives
- swelling of various parts of the body such as the face, lips, tongue, throat, hands or feet
- fever with joint pain
- trouble breathing, speaking or swallowing
- wheezing or shortness of breath

Get medical attention right away if you have trouble breathing, speaking or swallowing; wheezing; shortness of breath; or swelling of the mouth, tongue or throat.

Taking iodide, in rare cases, may cause overactivity of the thyroid gland, underactivity of the thyroid gland, or enlargement of the thyroid gland (goiter). Symptoms of an overactive thyroid gland may include an irregular heartbeat and chest pain. Patients with thyroid disease are more likely to get these side effects. Babies under 1 month of age are more likely to get an underactive thyroid gland (hypothyroidism).

WHAT TO DO IF SIDE EFFECTS OCCUR

Stop taking KI and call a doctor if you have one of the following symptoms:

- swelling of the face, hands or feet
- fever and joint pain
- skin rash

Stop taking KI and get medical help right away if you have one or more of the following symptoms:

- trouble breathing, speaking or swallowing
- shortness of breath or wheezing
- swelling of the lips, tongue or throat
- irregular heart beat or chest pain

HOW SUPPLIED

IOSAT™(Potassium Iodide Tablets, USP 65 mg) Packages of 20 tablets. Each white, round tablet, cross-scored on one side and the IOSAT name on the other, contains 65 mg potassium iodide.
NDC 51803-002-01: 2 X 10 Unit dose, Foil Sealed, 65 mg Tablets (20 Tablets).

IOSAT™(Potassium Iodide Tablets, USP 65 mg) Packages of 14 tablets. Each white, round tablet, cross-scored on one side and the IOSAT name on the other, contains 65 mg potassium iodide.
NDC 51803-002-02: 14 Unit dose, Foil Sealed, 65 mg Tablets (14 Tablets).

Also available: IOSAT™(Potassium Iodide Tablets, USP 130 mg) Each white, round tablet, cross-scored on one side and the IOSAT name on the other, contains 130 mg potassium iodide.
NDC 51803-001-01: 14 Unit dose, Foil Sealed, 130 mg Tablets.

STORAGE AND HANDLING

Store at 20-25°C (68-77°F). Keep dry and foil intact.

Distributed by:

ANBEX INC.
1812 West Sunset Blvd, Suite 1A-618
St George, UT 84770
(833) 467-2854
www.anbex.com
www.iosat.com

SH905-2
8/23

PRINCIPAL DISPLAY PANEL

IOSAT™ (Potassium Iodide Tablets, USP 65 mg)